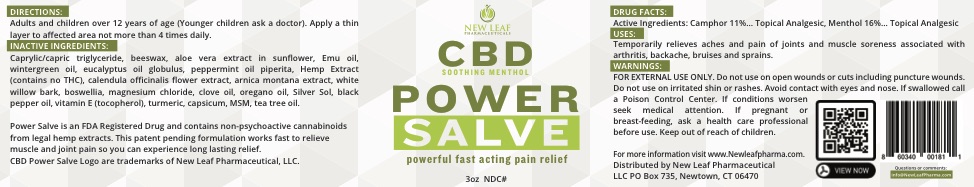 DRUG LABEL: PS
NDC: 71798-005 | Form: OINTMENT
Manufacturer: New Leaf Pharmaceutical, LLC
Category: otc | Type: HUMAN OTC DRUG LABEL
Date: 20200125

ACTIVE INGREDIENTS: MENTHOL, UNSPECIFIED FORM 16 g/16 mg
INACTIVE INGREDIENTS: PEPPERMINT OIL; BLACK PEPPER OIL; EUCALYPTUS GLOBULUS LEAF; CAMPHOR (SYNTHETIC); ALOE VERA LEAF; MAGNESIUM CHLORIDE; BOSWELLIA SERRATA WHOLE

CBD Power Salve